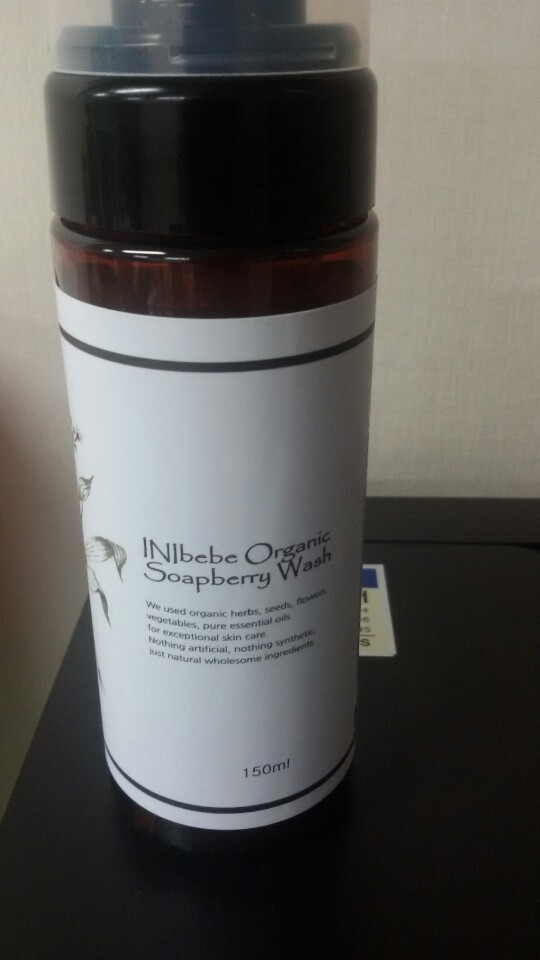 DRUG LABEL: INIbebe Organic Soapberry Wash
NDC: 69836-5001 | Form: LIQUID
Manufacturer: International Nature Soap Institute
Category: otc | Type: HUMAN OTC DRUG LABEL
Date: 20161018

ACTIVE INGREDIENTS: GLYCERIN 15 g/100 mL
INACTIVE INGREDIENTS: WATER; PANTHENOL; CITRIC ACID ACETATE

Drug Facts

ACTIVE INGREDIENT

glycerine

PURPOSE

skin protectant

keep out of reach of the children

INDICATIONS AND USAGE

apply to the skin and wash away

WARNINGS

・Stop using the product when you have skin problems or the product disagrees with your skin
・Stop using the product immediately and consult a dermatologist if you have redness, swelling, itching or irritation on the skin while or after using the product.
・If the product gets into the eyes, don't rub but rinse with water.
・Don't place the product in any place where it will be subjected to extremely high or low temperatures or direct sunlight.

DOSAGE AND ADMINISTRATION

for external use only

INACTIVE INGREDIENT

sodium chloride, citric acid, panthenol, water, etc